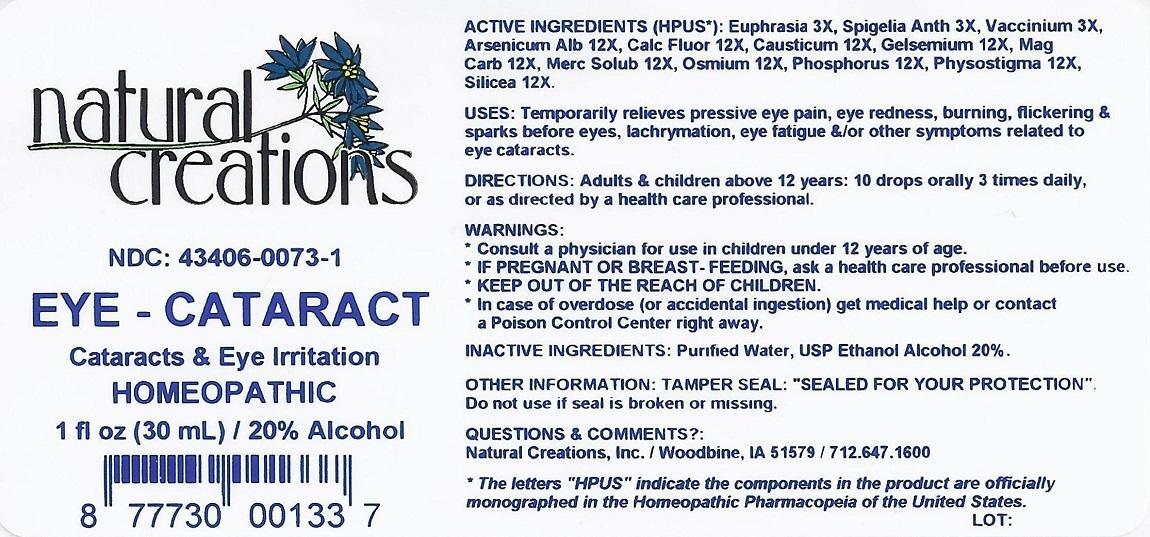 DRUG LABEL: EYE -  CATARACT
NDC: 43406-0073 | Form: LIQUID
Manufacturer: Natural Creations, Inc.
Category: homeopathic | Type: HUMAN OTC DRUG LABEL
Date: 20130130

ACTIVE INGREDIENTS: EUPHRASIA STRICTA 3 [hp_X]/1 mL; SPIGELIA ANTHELMIA 3 [hp_X]/1 mL; BILBERRY 3 [hp_X]/1 mL; ARSENIC TRIOXIDE 12 [hp_X]/1 mL; CALCIUM FLUORIDE 12 [hp_X]/1 mL; CAUSTICUM 12 [hp_X]/1 mL; GELSEMIUM SEMPERVIRENS ROOT 12 [hp_X]/1 mL; MAGNESIUM CARBONATE 12 [hp_X]/1 mL; MERCURIUS SOLUBILIS 12 [hp_X]/1 mL; OSMIUM 12 [hp_X]/1 mL; PHOSPHORUS 12 [hp_X]/1 mL; PHYSOSTIGMA VENENOSUM SEED 12 [hp_X]/1 mL; SILICON DIOXIDE 12 [hp_X]/1 mL
INACTIVE INGREDIENTS: WATER; ALCOHOL

EYE - CATARACT

ACTIVE INGREDIENT

ACTIVE INGREDIENTS (HPUS*): Euphrasia Officinalis 3X, Spigelia Anthelmia 3X, Vaccinium Myrtillus 3X, Arsenicum Album 12X, Calcarea Fluorica 12X, Causticum 12X, Gelsemium Sempervirens 12X, Magnesia Carbonica 12X, Mercurius Solubilis 12X, Osmium Metallicum 12X, Phosphorus 12X, Physostigma Venenosum 12X, Silicea 12X

PURPOSE

USES: Temporarily relieves pressive eye pain, eye redness, burning, flickering & sparks before eyes, lachrymation, eye fatigue &/or other symptoms related to eye cataracts.

INDICATIONS AND USAGE

USES: Temporarily relieves pressive eye pain, eye redness, burning, flickering & sparks before eyes, lachrymation, eye fatigue &/or other symptoms related to eye cataracts.

DOSAGE AND ADMINISTRATION

Directions: Adults & children above 12 years: 10 drops orally 3 times daily, or as directed by a health care professional.

WARNINGS:

*Consult a physician for use in children under 12 years of age.

* IF PREGNANT OR BREAST-FEEDING, ask a health care professional before use.

* KEEP OUT OF THE REACH OF CHILDREN. In case of overdose (or accidental ingestion) get medical help or contact a Poison Control Center right away.

WARNINGS:

*Consult a physician for use in children under 12 years of age.

* IF PREGNANT OR BREAST-FEEDING, ask a health care professional before use.

* KEEP OUT OF THE REACH OF CHILDREN. In case of overdose (or accidental ingestion) get medical help or contact a Poison Control Center right away.

Inactive Ingredients: Purified Water, USP Ethanol Alcohol 20%

Other Information: Tamper Seal: “Sealed for your protection.” Do not use if seal is broken or missing.

QUESTIONS

Questions & Comments? Natural Creations, Inc. / Woodbine, IA 51579 / 712.647.1600

*The letters “HPUS” indicate the components in the product are officially monographed in the Homeopathic Pharmacopeia of the United States.

PACKAGE LABEL

NDC: 43406-0073-1

EYE - CATARACT

Cataracts & Eye Irritation

HOMEOPATHIC

1 fl oz (30 mL) 20% Alcohol

UPC: 877730001337